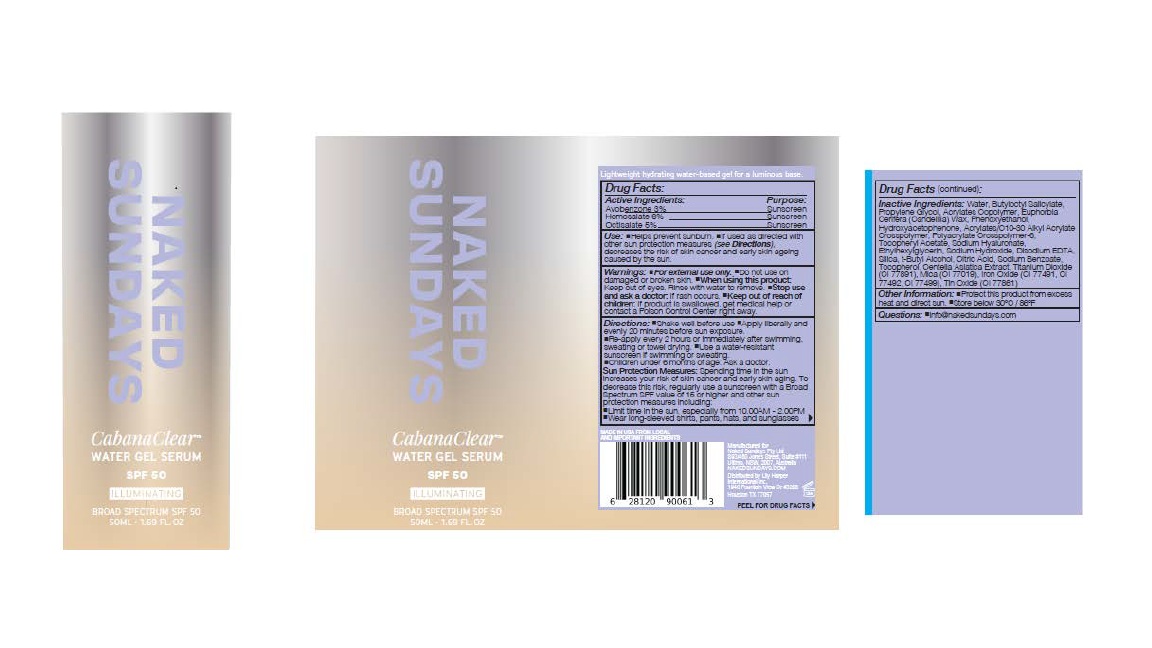 DRUG LABEL: CabanaClear Illuminating
NDC: 81104-594 | Form: LOTION
Manufacturer: NAKED SUNDAYS PTY LTD
Category: otc | Type: HUMAN OTC DRUG LABEL
Date: 20251221

ACTIVE INGREDIENTS: OCTISALATE 5 g/100 mL; HOMOSALATE 6 g/100 mL; AVOBENZONE 3 g/100 mL
INACTIVE INGREDIENTS: ACRYLATES/C10-30 ALKYL ACRYLATE CROSSPOLYMER (60000 MPA.S); SILICA; BUTYLOCTYL SALICYLATE; EUPHORBIA CERIFERA (CANDELILLA) WAX; EDETATE DISODIUM; MICA; CI 77491; CI 77492; SODIUM HYDROXIDE; ETHYLHEXYLGLYCERIN; CITRIC ACID; HYDROXYACETOPHENONE; POLYACRYLATE CROSSPOLYMER-6; WATER; SODIUM BENZOATE; PROPYLENE GLYCOL; BUTYL ACRYLATE/METHYL METHACRYLATE/METHACRYLIC ACID COPOLYMER (18000 MW); PHENOXYETHANOL; ALPHA-TOCOPHEROL ACETATE; SODIUM HYALURONATE; CENTELLA ASIATICA TRITERPENOIDS; CI 77891; CI 77499; TIN OXIDE

CabanaClear Illuminating

ACTIVE INGREDIENT

Active Ingredients (% W/W): Avobenzone 3%, Homosalate 6%, Octyl Salicylate 5%

PURPOSE

Sunscreen

Use:

• Helps prevent sunburn.

• If used as directed with other sun protection measures (see Directions), decreases the risk of skin cancer and early skin ageing caused by the sun

Warnings: For external use only.

• Do not use on damaged or broken skin.

• When using this product: Keep out of eyes. Rinse with water to remove.

• Stop use and ask a doctor: If rash occurs.

• Keep out of reach of children: If product is swallowed, get medical help or contact a Poison Control Center right away

Directions:

• Shake well before use.

• Apply liberally and evenly 20 minutes before sun exposure.

• Re-apply every 2 hours or immediately after swimming, sweating or towel drying.

• Use a water-resistant sunscreen if swimming or sweating.

Children under 6 months of age: Ask a doctor

Sun Protection Measures: Spending time in the sun increases your risk of skin cancer and early skin aging. To decrease this risk, regularly use a sunscreen with a Broad Spectrum SPF value of 15 or higher and other sun protection measures including:

• Limit time in the sun, especially from 10.00AM - 2.00PM

• Wear long-sleeved shirts, pants, hats, and sunglasses

Other Information:

• Protect this product from excess heat and direct sun.

• Store below 30°C / 86°F

Questions:

• info@nakedSundays.com

INACTIVE INGREDIENT

Inactive Ingredients: Water, Butyloctyl Salicylate, Propylene Glycol, Acrylates Copolymer, Euphorbia Cerifera (Candelilla) Wax, Phenoxyethanol, Hydroxyacetophenone, Acrylates/C10-30 Alkyl Acrylate Crosspolymer, Polyacrylate Crosspolymer-6, Tocopheryl Acetate, Sodium Hyaluronate, Ethylhexylglycerin, Sodium Hydroxide, Disodium EDTA, Silica, t-Butyl Alcohol, Citric Acid, Sodium Benzoate, Tocopherol, Centella Asiatica Extract, Titanium Dioxide (CI 77891), Mica (CI 77019), Iron Oxide (CI 77491, CI 77492, CI 77499), Tin Oxide (CI 77861)